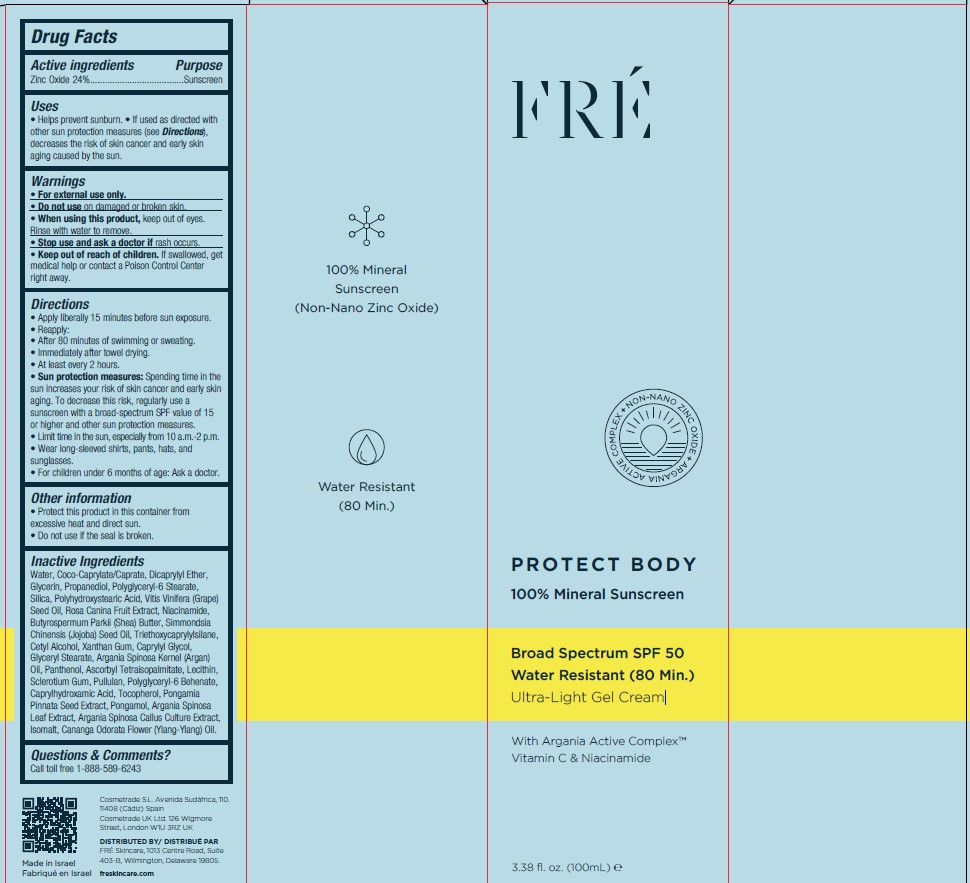 DRUG LABEL: FRE PROTECT BODY  Ultra-Light Gel Cream SPF 50
NDC: 69435-1412 | Form: JELLY
Manufacturer: Peer Pharm Ltd.
Category: otc | Type: HUMAN OTC DRUG LABEL
Date: 20250130

ACTIVE INGREDIENTS: ZINC OXIDE 24 g/100 mL
INACTIVE INGREDIENTS: WATER; COCO-CAPRYLATE/CAPRATE; DICAPRYLYL ETHER; GLYCERIN; PROPANEDIOL; POLYGLYCERYL-6 STEARATE; SILICA; POLYHYDROXYSTEARIC ACID (2300 MW); GRAPE SEED OIL; ROSA CANINA FRUIT; NIACINAMIDE; SHEA BUTTER; JOJOBA OIL; TRIETHOXYCAPRYLYLSILANE; CETYL ALCOHOL; XANTHAN GUM; CAPRYLYL GLYCOL; GLYCERYL STEARATE; PANTHENOL; ARGAN OIL; ASCORBYL TETRAISOPALMITATE; LECITHIN, SOYBEAN; SCLEROTIUM GUM; PULLULAN; POLYGLYCERYL-6 BEHENATE; CAPRYLHYDROXAMIC ACID; TOCOPHEROL; PONGAMIA PINNATA SEED; PONGAMOL; ARGANIA SPINOSA LEAF; ISOMALT; YLANG-YLANG OIL

FRE PROTECT BODY Ultra-Light Gel Cream SPF 50

Active ingredients

Zinc Oxide 24%

Purpose

Sunscreen

Uses

Helps prevent sunburn. • If used as directed with
other sun protection measures (see Directions),
decreases the risk of skin cancer and early skin
aging caused by the sun.

Warnings

• For external use only.
• Do not use on damaged or broken skin.
• When using this product, keep out of eyes.
Rinse with water to remove.
• Stop use and ask a doctor if rash occurs.
• Keep out of reach of children. If swallowed, get
medical help

Inactive Ingredients

Water, Coco-Caprylate/Caprate, Dicaprylyl Ether,
Glycerin, Propanediol, Polyglyceryl-6 Stearate,
Silica, Polyhydroxystearic Acid, Vitis Vinifera (Grape)
Seed Oil, Rosa Canina Fruit Extract, Niacinamide,
Butyrospermum Parkii (Shea) Butter, Simmondsia
Chinensis (Jojoba) Seed Oil, Triethoxycaprylylsilane,
Cetyl Alcohol, Xanthan Gum, Caprylyl Glycol,
Glyceryl Stearate, Argania Spinosa Kernel (Argan)
Oil, Panthenol, Ascorbyl Tetraisopalmitate, Lecithin,
Sclerotium Gum, Pullulan, Polyglyceryl-6 Behenate,
Caprylhydroxamic Acid, Tocopherol, Pongamia
Pinnata Seed Extract, Pongamol, Argania Spinosa
Leaf Extract, Argania Spinosa Callus Culture Extract,
Isomalt, Cananga Odorata Flower (Ylang-Ylang) Oil.

Directions

• Apply liberally 15 minutes before sun exposure.
• Reapply:
• After 80 minutes of swimming or sweating.
• Immediately after towel drying.
• At least every 2 hours.
• Sun protection measures: Spending time in the
sun increases your risk of skin cancer and early skin
aging. To decrease this risk, regularly use a
sunscreen with a broad-spectrum SPF value of 15
or higher and other sun protection measures.
• Limit time in the sun, especially from 10 a.m.-2 p.m.
• Wear long-sleeved shirts, pants, hats, and
sunglasses.
• For children under 6 months of age: Ask a doctor.

Other information

Protect this product in this container from
excessive heat and direct sun.
• Do not use if the seal is broken.

Questions & Comments?

Call toll free 1-888-589-6243